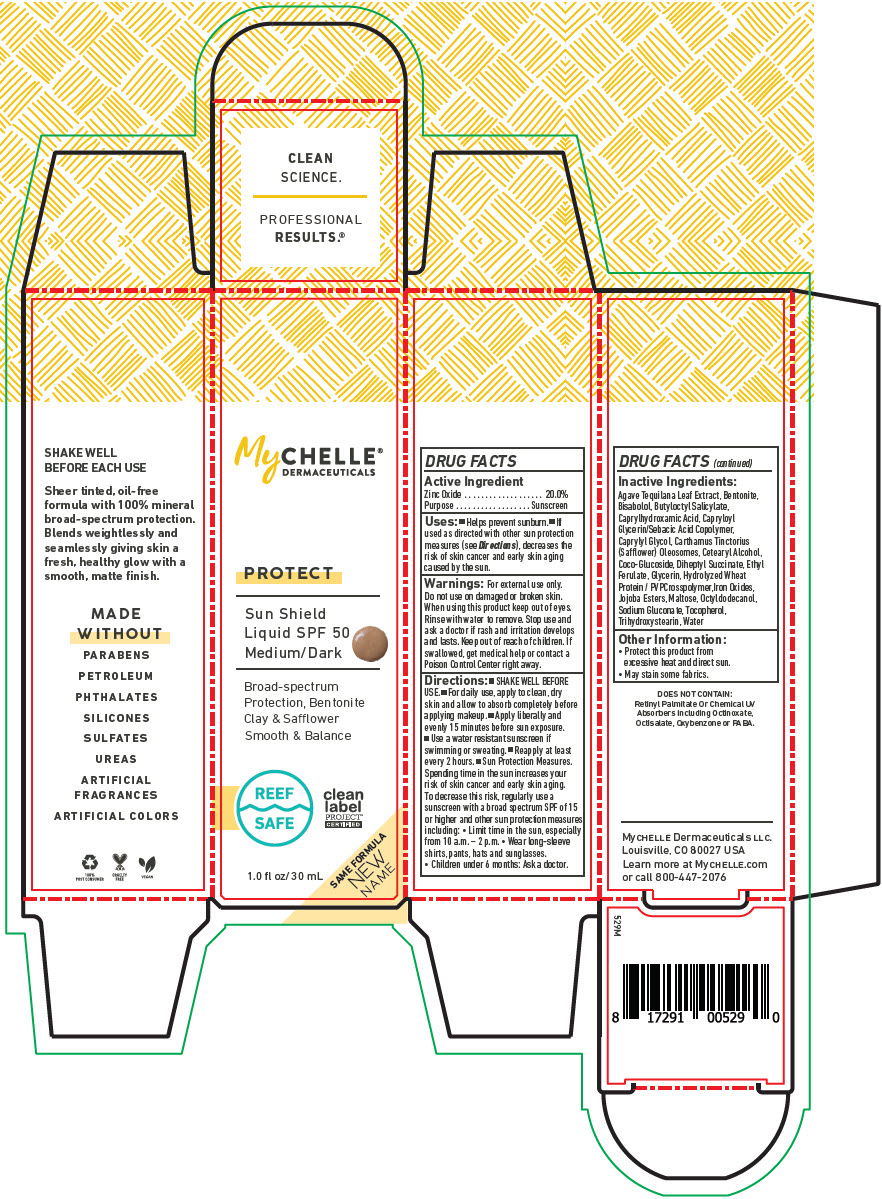 DRUG LABEL: MyChelle Dermaceuticals Sun Shield SPF 50 Medium/Dark 
NDC: 72805-200 | Form: LIQUID
Manufacturer: French Transit, Ltd.
Category: otc | Type: HUMAN OTC DRUG LABEL
Date: 20210325

ACTIVE INGREDIENTS: Zinc Oxide 20 g/100 mL
INACTIVE INGREDIENTS: Water; AGAVE TEQUILANA LEAF; Bentonite; LEVOMENOL; Butyloctyl Salicylate; Caprylhydroxamic Acid; CAPRYLOYL GLYCERIN/SEBACIC ACID COPOLYMER (2000 MPA.S); Caprylyl Glycol; CARTHAMUS TINCTORIUS SEED OLEOSOMES; CETOSTEARYL ALCOHOL; COCO GLUCOSIDE; Diheptyl Succinate; Ethyl Ferulate; GLYCERIN; HYDROLYZED WHEAT PROTEIN (ENZYMATIC; 3000 MW); FERRIC OXIDE RED; HYDROGENATED JOJOBA OIL, RANDOMIZED; MALTOSE, UNSPECIFIED FORM; Octyldodecanol; Sodium Gluconate; TOCOPHEROL; Trihydroxystearin

MyChelle® Dermaceuticals Sun Shield SPF 50 Medium/Dark
Protect

DRUG FACTS

Active Ingredient

Zinc Oxide 20.0%

Purpose

Sunscreen

Uses

- Helps prevent sunburn.
- If used as directed with other sun protection measures (see Directions), decreases the risk of skin cancer and early skin aging caused by the sun.

Warnings

For external use only.

Do not use on damaged or broken skin.

When using this product keep out of eyes.

Rinse with water to remove. Stop use and ask a doctor if rash and irritation develops and lasts.

Keep out of reach of children. If swallowed, get medical help or contact a Poison Control Center right away.

Directions

- SHAKE WELL BEFORE USE.
- For daily use, apply to clean, dry skin and allow to absorb completely before applying makeup.
- Apply liberally and evenly 15 minutes before sun exposure.
- Use a water resistant sunscreen if swimming or sweating.
- Reapply at least every 2 hours.
- Sun Protection Measures. Spending time in the sun increases your risk of skin cancer and early skin aging. To decrease this risk, regularly use a sunscreen with a broad spectrum SPF of 15 or higher and other sun protection measures including:
  - Limit time in the sun, especially from 10 a.m. – 2 p.m.
  - Wear long-sleeve shirts, pants, hats and sunglasses.
  - Children under 6 months: Ask a doctor.

Inactive Ingredients

Agave Tequilana Leaf Extract, Bentonite, Bisabolol, Butyloctyl Salicylate, Caprylhydroxamic Acid, Capryloyl Glycerin/Sebacic Acid Copolymer, Caprylyl Glycol, Carthamus Tinctorius (Safflower) Oleosomes, Cetearyl Alcohol, Coco-Glucoside, Diheptyl Succinate, Ethyl Ferulate, Glycerin, Hydrolyzed Wheat Protein / PVPCrosspolymer,Iron Oxides, Jojoba Esters, Maltose, Octyldodecanol, Sodium Gluconate, Tocopherol, Trihydroxystearin, Water

Other Information

- Protect this product from excessive heat and direct sun.
- May stain some fabrics.

PRINCIPAL DISPLAY PANEL - 30 mL Bottle Box

MyCHELLE®
DERMACEUTICALS

PROTECT

Sun Shield
Liquid SPF 50
Medium/Dark

Broad-spectrum
Protection, Bentonite
Clay & Safflower
Smooth & Balance

REEF
SAFE

clean
label
PROJECT®
CERTIFIED

SAME FORMULA
NEW
NAME

1.0 fl oz/30 mL